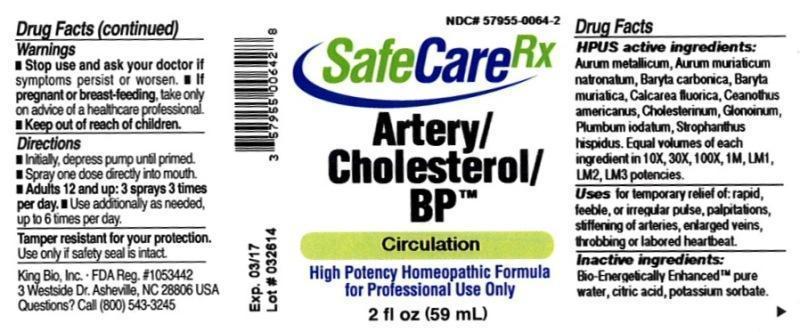 DRUG LABEL: Artery/Cholesterol/BP
NDC: 57955-0064 | Form: LIQUID
Manufacturer: King Bio Inc.
Category: homeopathic | Type: HUMAN OTC DRUG LABEL
Date: 20140417

ACTIVE INGREDIENTS: GOLD 10 [hp_X]/59 mL; SODIUM TETRACHLOROAURATE 10 [hp_X]/59 mL; BARIUM CARBONATE 10 [hp_X]/59 mL; BARIUM CHLORIDE DIHYDRATE 10 [hp_X]/59 mL; CALCIUM FLUORIDE 10 [hp_X]/59 mL; CEANOTHUS AMERICANUS LEAF 10 [hp_X]/59 mL; CHOLESTEROL 10 [hp_X]/59 mL; NITROGLYCERIN 10 [hp_X]/59 mL; LEAD IODIDE 10 [hp_X]/59 mL; STROPHANTHUS HISPIDUS SEED 10 [hp_X]/59 mL
INACTIVE INGREDIENTS: WATER; CITRIC ACID MONOHYDRATE; POTASSIUM SORBATE

Artery/Cholesterol/BP™

ACTIVE INGREDIENT

Drug Facts__________________________________________________________________________________________________________

HPUS activeingredients: Aurum metallicum, Aurum muriaticum natronatum, Baryta carbonica, Baryta muriatica, Calcarea fluorica, Ceanothus americanus, Cholesterinum, Glonoinum, Plumbum iodatum, Strophanthus hispidus. Equal volumes of each ingredient in 10X, 30X, 100X,1M LM1, LM2, LM3 potencies.

INDICATIONS AND USAGE

Uses for temporary relief of: rapid, feeble, or irregular pulse, palpitations, stiffening of arteries, enlarged veins, throbbing or labored heartbeat.

Inactive Ingredients:

Bio-Energetically Enhanced™ pure water, citric acid and potassium sorbate.

Warnings

- Stop use and ask your doctor if symptoms persist or worsen.
- If pregnant or breast-feeding, take only on advice of a healthcare professional.

- Keep out of reach of children

Directions

- Initially, depress pump until primed.
- Spray one dose directly into mouth.
- Adults 12 and up: 3 sprays 3 times per day.
- Use additionally as needed, up to 6 times per day.

OTHER SAFETY INFORMATION

Tamper resistant for your protection. Use only if safety seal is intact.

PURPOSE

Uses for temporary relief of:

- rapid, feeble, or irregular pulse
- palpitations
- stiffening of arteries
- enlarged veins
- throbbing or labored heartbeat